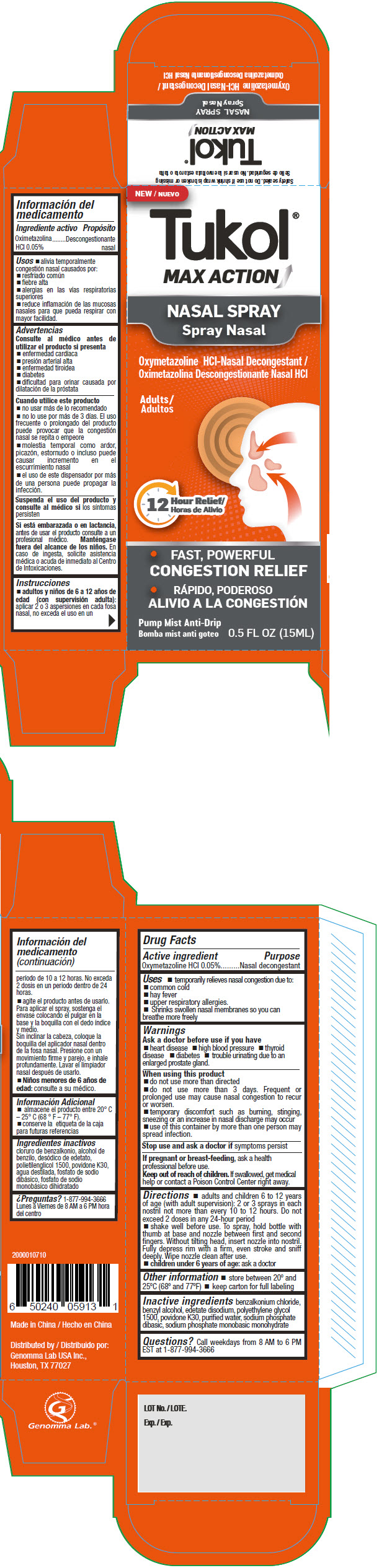 DRUG LABEL: Tukol Max Action
NDC: 50066-307 | Form: LIQUID
Manufacturer: Genomma Lab USA
Category: otc | Type: HUMAN OTC DRUG LABEL
Date: 20210722

ACTIVE INGREDIENTS: oxymetazoline hydrochloride 0.5 mg/1 mL
INACTIVE INGREDIENTS: benzalkonium chloride; Water; Benzyl alcohol; SODIUM PHOSPHATE, DIBASIC, ANHYDROUS; SODIUM PHOSPHATE, MONOBASIC, ANHYDROUS; Edetate disodium

Tukol® Max Action Nasal Spray

Drug Facts

Active ingredient

Oxymetazoline HCl 0.05%

Purpose

Nasal decongestant

Uses

- temporarily relieves nasal congestion due to:
  - common cold
  - hay fever
  - upper respiratory allergies.
  - Shrinks swollen nasal membranes so you can breathe more freely

Warnings

Ask a doctor before use if you have

- heart disease
- high blood pressure
- thyroid disease
- diabetes
- trouble urinating due to an enlarged prostate gland.

When using this product

- do not use more than directed
- do not use more than 3 days. Frequent or prolonged use may cause nasal congestion to recur or worsen.
- temporary discomfort such as burning, stinging, sneezing or an increase in nasal discharge may occur
- use of this container by more than one person may spread infection.

Stop use and ask a doctor if symptoms persist

PREGNANCY OR BREAST FEEDING

If pregnant or breast-feeding, ask a health professional before use.

Keep out of reach of children. If swallowed, get medical help or contact a Poison Control Center right away.

Directions

- adults and children 6 to 12 years of age (with adult supervision): 2 or 3 sprays in each nostril not more than every 10 to 12 hours. Do not exceed 2 doses in any 24-hour period
- shake well before use. To spray, hold bottle with thumb at base and nozzle between first and second fingers. Without tilting head, insert nozzle into nostril. Fully depress rim with a firm, even stroke and sniff deeply. Wipe nozzle clean after use.
- children under 6 years of age: ask a doctor

Other information

- store between 20° and 25°C (68° and 77°F)
- keep carton for full labeling

Inactive ingredients

benzalkonium chloride, benzyl alcohol, edetate disodium, polyethylene glycol 1500, povidone K30, purified water, sodium phosphate dibasic, sodium phosphate monobasic monohydrate

Questions?

Call weekdays from 8 AM to 6 PM EST at 1-877-994-3666

Distributed by
Genomma Lab USA Inc.,
Houston, TX 77027

PRINCIPAL DISPLAY PANEL - 15 ML Bottle Carton

NEW

Tukol®
MAX ACTION

NASAL SPRAY
Spray Nasal

Oxymetazoline HCl-Nasal Decongestant

Adults

12
Hour Relief

- FAST, POWERFUL
  CONGESTION RELIEF

Pump Mist Anti-Drip

0.5 FL OZ (15ML)